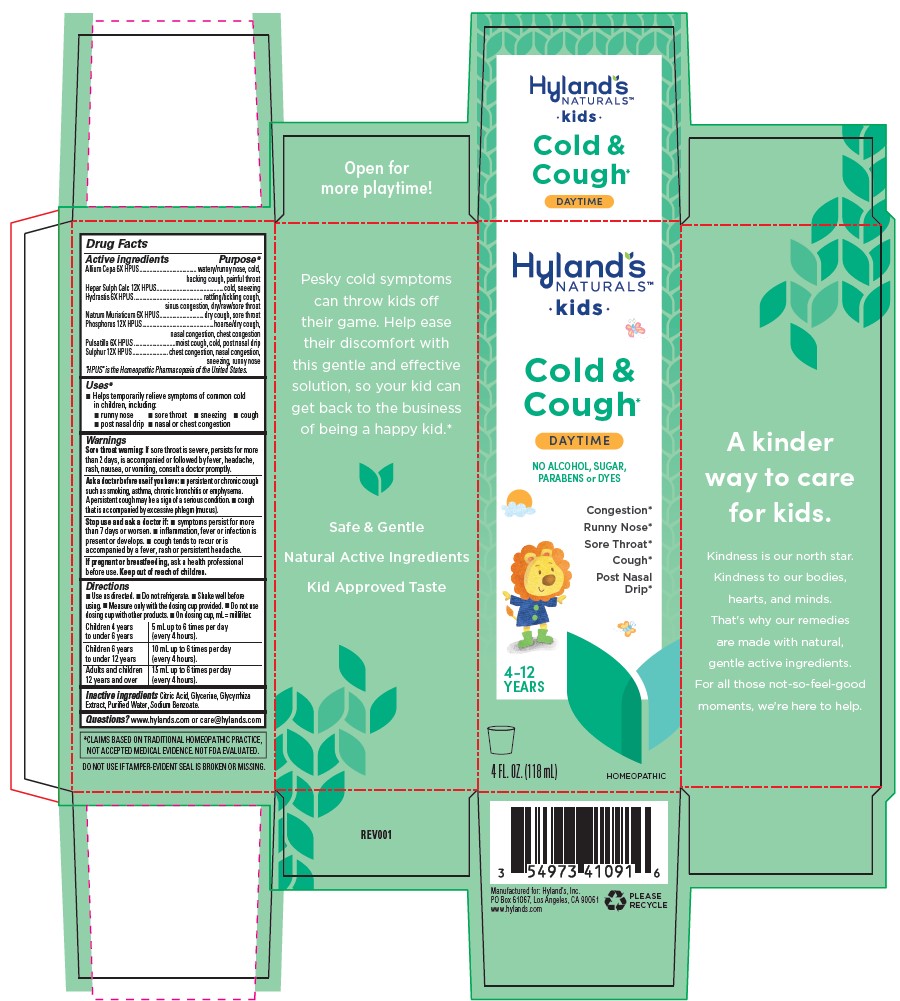 DRUG LABEL: Kids Cold and Cough Daytime
NDC: 54973-4109 | Form: LIQUID
Manufacturer: Hyland's Consumer Health Inc.
Category: homeopathic | Type: HUMAN OTC DRUG LABEL
Date: 20251219

ACTIVE INGREDIENTS: SODIUM CHLORIDE 6 [hp_X]/1 mL; ONION 6 [hp_X]/1 mL; GOLDENSEAL 6 [hp_X]/1 mL; PHOSPHORUS 12 [hp_X]/1 mL; PULSATILLA VULGARIS 6 [hp_X]/1 mL; SULFUR 12 [hp_X]/1 mL; CALCIUM SULFIDE 12 [hp_X]/1 mL
INACTIVE INGREDIENTS: CITRIC ACID MONOHYDRATE; WATER; SODIUM BENZOATE; GLYCERIN; GLYCYRRHIZA GLABRA

Hyland's Naturals Kids Cold & Cough Daytime

PURPOSE

Runny Nose, Sore Throat, Sneezing, Cough, Post Nasal Drip, Aasal or Chest Congestion

Drug Facts

Active ingredients | Purpose*
Allium Cepa 6X HPUS........................................... | watery/runny nose, cold, hacking cough, painful throat
Hepar Sulph Calc 12X HPUS.............................................. | cold, sneezing
Hydrastis 6X HPUS................................................ | rattling/tickling cough, sinus congestion, dry/raw/sore throat
Natrum Muriaticum 6X HPUS............................... | dry cough, sore throat
Phosphorus 12X HPUS.................................................. | hoarse/dry cough, nasal congestion, chest congestion
Pulsatilla 6X HPUS ............................. | moist cough, cold, post nasal drip
Sulphur 12X HPUS......................... | chest congestion, nasal congestion, sneezing, runny nose

"HPUS" is the Homeopathic Pharmacopoeia of the United States.

Uses*

■ Helps temporarily relieve symptoms of common cold in children, including:

■ runny nose ■ sore throat ■ sneezing ■ cough
■ post nasal drip ■ nasal or chest congestion

Warnings

Sore throat warning

If sore throat is severe, persists for more than 2 days, is accompanied or followed by fever, headache, rash, nausea, or vomiting, consult a doctor promptly.

Ask a doctor before use if you have

■ persistent or chronic cough such as smoking, asthma, chronic bronchitis or emphysema. A persistent cough may be a sign of a serious condition. ■ cough that is accompanied by excessive phlegm (mucus).

Stop use and ask a doctor if

■ symptoms persist for more than 7 days or worsen. ■ inflammation, fever or infection is present or develops. ■ cough tends to recur or is accompanied by a fever, rash or persistent headache.

If pregnant or breastfeeding

Ask a health professional before use.

Directions

■ Use as directed. ■ Do not refrigerate. ■ Shake well before using. ■ Measure only with the dosing cup provided. ■ Do not use
dosing cup with other products. ■ On dosing cup, mL = milliliter.

Children 4 years to under 6 years | 5 mL up to 6 times per day (every 4 hours).
Children 6 years to under 12 years | 10 mL up to 6 times per day (every 4 hours).
Adults and children 12 years and over | 15 mL up to 6 times per day (every 4 hours).

Inactive ingredients

Citric Acid, Glycerine, Glycyrrhiza Extract, Purified Water, Sodium Benzoate.

Questions?

www.hylands.com or care@hylands.com

Indications and Usage

Uses*

Principal Display Panel

Hyland's

NATURALS™

•Kids•

Cold &

Cough*

DAYTIME

NO ALCOHOL, SUGAR,

PARABENS or DYES

Congestion*

Runny Nose*

Sore Throat*

Cough*

Post Nasal

Drip*

4 - 12

YEARS

4 FL. OZ. (118 mL)

HOMEOPATHIC